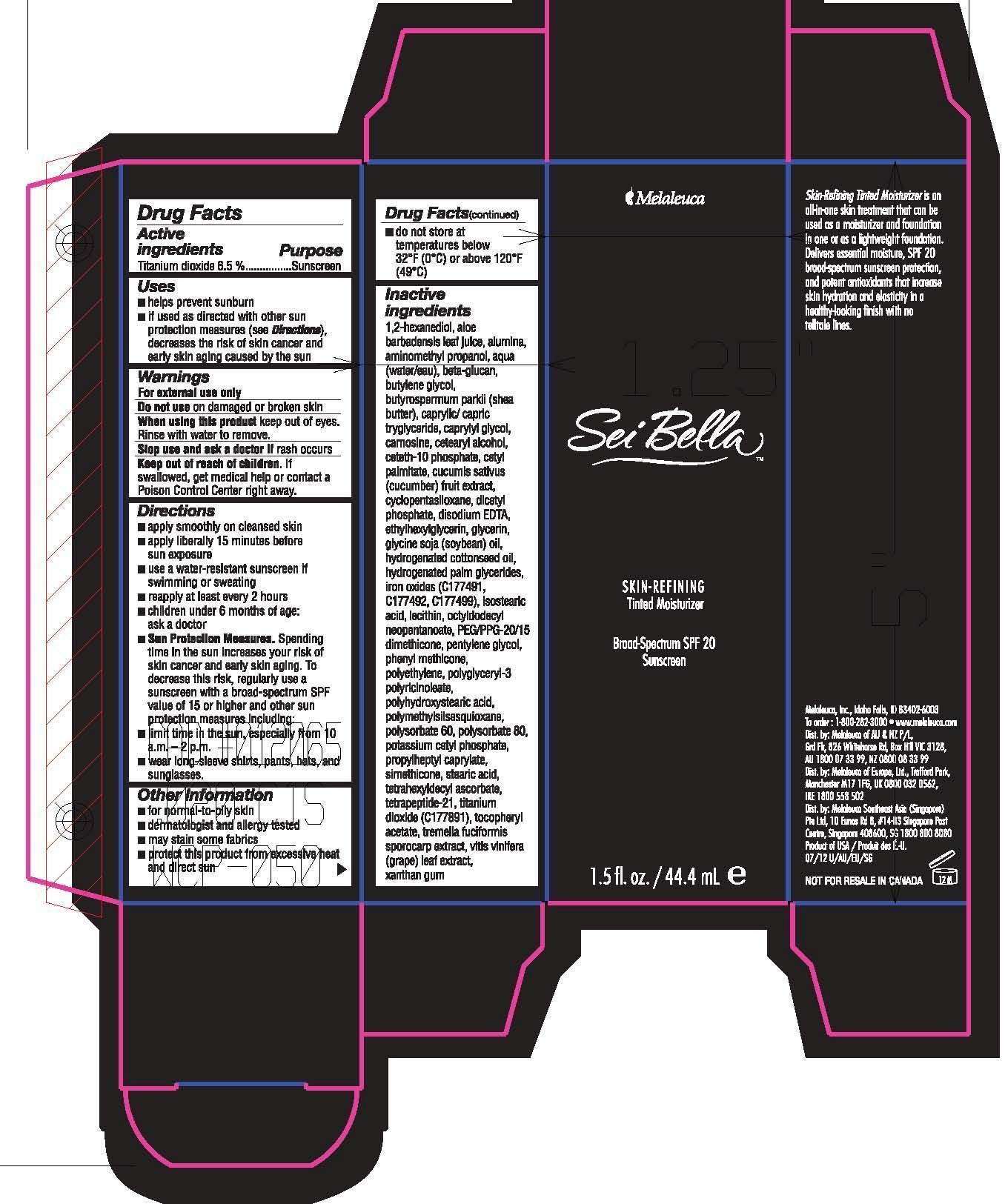 DRUG LABEL: Sei Bella Skin Refining Tinted Moisturizer
NDC: 54473-247 | Form: LOTION
Manufacturer: Melaleuca Inc.
Category: otc | Type: HUMAN OTC DRUG LABEL
Date: 20140430

ACTIVE INGREDIENTS: TITANIUM DIOXIDE 2.866 g/44.4 mL
INACTIVE INGREDIENTS: 1,2-HEXANEDIOL; ALOE VERA LEAF; ALUMINUM OXIDE; AMINOMETHYLPROPANOL; BUTYLENE GLYCOL; SHEA BUTTER; MEDIUM-CHAIN TRIGLYCERIDES; CAPRYLYL GLYCOL; CARNOSINE; CETOSTEARYL ALCOHOL; CETETH-10 PHOSPHATE; CETYL PALMITATE; CUCUMBER; CYCLOMETHICONE 5; DIHEXADECYL PHOSPHATE; EDETATE DISODIUM; ETHYLHEXYLGLYCERIN; glycerin; SOYBEAN OIL; HYDROGENATED COTTONSEED OIL; HYDROGENATED PALM GLYCERIDES; ISOSTEARIC ACID; LECITHIN, SOYBEAN; OCTYLDODECYL NEOPENTANOATE; PEG/PPG-20/15 DIMETHICONE; PENTYLENE GLYCOL; HIGH DENSITY POLYETHYLENE; POLYGLYCERYL-3 RICINOLEATE; POLYHYDROXYSTEARIC ACID (2300 MW); POLYMETHYLSILSESQUIOXANE (4.5 MICRONS); POLYSORBATE 60; POLYSORBATE 80; POTASSIUM CETYL PHOSPHATE; PROPYLHEPTYL CAPRYLATE; STEARIC ACID; TETRAHEXYLDECYL ASCORBATE; TETRAPEPTIDE-21; ALPHA-TOCOPHEROL ACETATE; TREMELLA FUCIFORMIS FRUITING BODY; VITIS VINIFERA LEAF; XANTHAN GUM; FERRIC OXIDE YELLOW; FERRIC OXIDE RED; FERROSOFERRIC OXIDE

Sei Bella Skin-Refining Tinted Moisturizer - Broadspectrum SPF 20 - Procelain

Active Ingredients

Titanium Dioxide 6.5%

Purpose

Sunscreen

Uses

- helps prevent sunburn
- is used as directed with other sun protection measures (see Directions), decreases the risk of skin cancer and early skin aging caused by the sun

Warnings

For External Use Only

Do not use on damaged or broken skin

When using this product keep out of eyes. Rinse with water to remove.

Stop use and ask a doctor if rash occurs

KEEP OUT OF REACH OF CHILDREN

Keep out of the reach of children. If swallowed, get medical help or contact a Poison Control Center right away.

Directions

- apply smoothly on cleased skin
- apply liberally 15 minutes before sun exposure
- use a water-resistant sunscreen if swimming or sweating
- reapply at least every 2 hours
- children under 6 months of age: ask a doctor
- Sun Protection Measures: Spending time in the sun increases your risk of skin cancer and early skin aging. To decrease this risk, regularly use a sunscreen with a broad-spectrum SPF value of 15 or higher and other sun protection measures including:
- limit time in the sun, especially from 10a.m.-2p.m.
- wear long-sleeve shirts, pants, hats, and sunglasses

Other Information

for normal-to-oily skin

CLINICAL STUDIES

dermatologist and allergy tested

STORAGE AND HANDLING

- may stain some fabrics
- protect this product from excessive heat and direct sun
- do not store at temperatures below 32oF (0oC) or above 120oF (49oC)

Inactive Ingredients

1,2-hexandiol, aloe barbadensis leaf juice, alumina, aminomethyl propanol, aqua (water/eau), beta-glucan, butylene glycol, butyrospermum parkii (shea butter), caprylic/capric tryglyceride, caprylyl glycol, carnosine, cetearyl alcohol, ceteth-10 phosphate, cetyl palmitate, cucumis sativus (cucumber) fruit extract, cyclopentasilloxane, dicetyl phosphate, disodium EDTA, ethylhexylglycerin, glycerin, glycine soja (soybean) oil, hydrogenated cottonseed oil, hydrogenated palm glycerides, iron oxides (CI77491, CI77492, CI77499), isostearic acid, lecithin, octyldodecyl neopentanoate, PEG/PPG-20/15 dimethicone, pentylene glycol, phenyl methicone, polyethylene, polyglyceryl-3, polyricinoleate, polyhydroxystearic acid, polymethylsilsesquioxane, polysorbate 60, polysorbate 80, potassium cetyl phosphate, propylheptyl caprylate, simethicone, stearic acid, tetrahexyldecyl ascorbate, tetrapeptide-21, titanium dioxide (CI77891), tocopheryl acetate, tremella fuciformis sporocarp extract, vitis vinifera (grape) leaf extract, xanthan gum